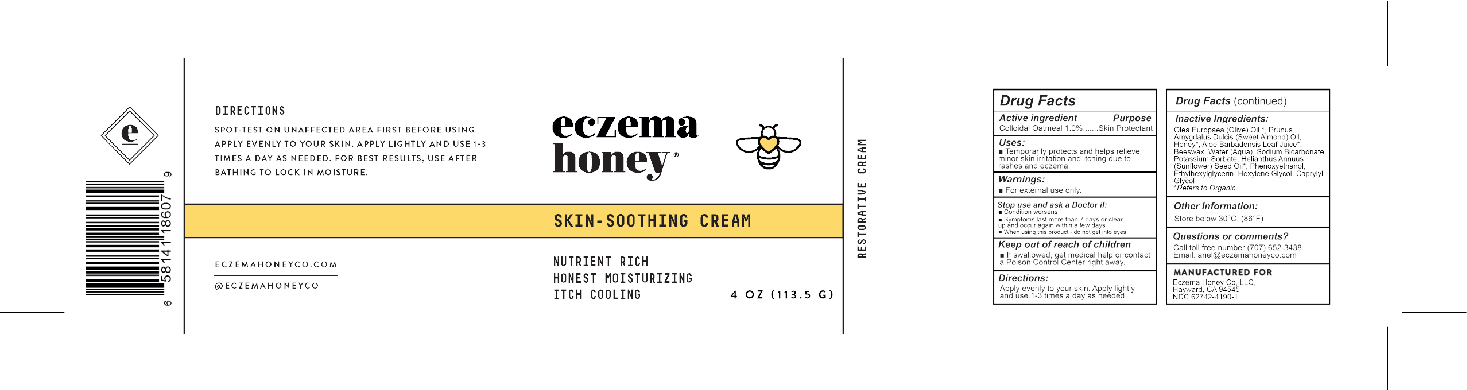 DRUG LABEL: Skin Soothing Cream
NDC: 62742-4190 | Form: CREAM
Manufacturer: Allure Labs Inc
Category: otc | Type: HUMAN OTC DRUG LABEL
Date: 20241205

ACTIVE INGREDIENTS: OATMEAL 1 mg/1 g
INACTIVE INGREDIENTS: OLEA EUROPAEA (OLIVE) OIL UNSAPONIFIABLES; ALMOND OIL; HONEY; ALOE VERA LEAF; YELLOW WAX; WATER; SODIUM BICARBONATE; POTASSIUM SORBATE; SUNFLOWER OIL; PHENOXYETHANOL; ETHYLHEXYLGLYCERIN; HEXYLENE GLYCOL; CAPRYLYL GLYCOL

DRUG FACTS

Active Ingredients:

Colloidal Oatmeal 1%

Purpose: Skin Protectant

Uses:

- Temporarily protects and helps relieve minor skin irritation and itiching du to rashes and eczema.

WARNINGS

Warning: For external use only.

Stop use and ask a doctor: If condition worsens. Symptons last more than 7 days or clear up and appear again within a few days.

When using this product - do not get into eyes.

Keep out of reach of children: If swallowed, get medical help or contact a Poison Control Center right away.

Directions:

- Apply evenly to your skin. Apply lightly and use use 1-3 tomes a day as needed.

Other Information: Store below 30 C (68 F).

INACTIVE INGREDIENT

Inactive Ingredients: Olea Europaea (Olive) Oil, Prunus Amygdalus Dulcis (Sweet Almond) Oil, hHoney, Aloe Barbadensis Leaf juice, Beeswax, Water (Aqua), Sodium Bicarbonate, Potassium Sorbate, Helianthus Annus (Sunflower) Seed Oil, Phenoxyethanol, Ethylhexylglycerin, Hexylene Glycol, Caprylyl Glycol.

Questions or Comments?

Call toll free 707-652-3438

mail: ariel@eczemahoneyco.com

PACKAGE LABEL

Manufactured For

Eczema Honey CO LLC.

Hayward, CA, 94545